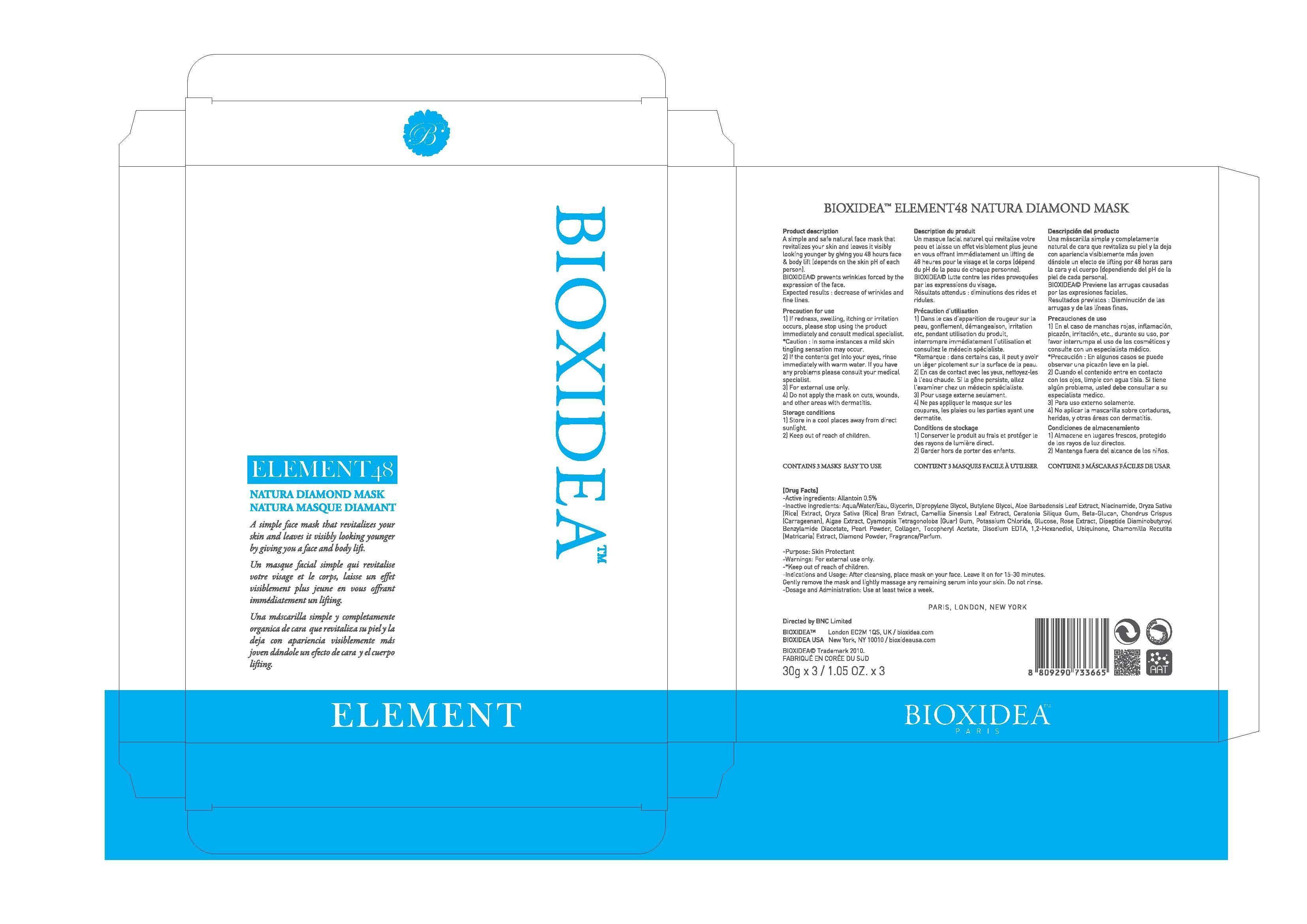 DRUG LABEL: BIOXIDEA ELEMENT 48 NATURA DIAMOND MASK
NDC: 69133-030 | Form: PATCH
Manufacturer: Cosmetics Institute Technology Co., Ltd.
Category: otc | Type: HUMAN OTC DRUG LABEL
Date: 20140827

ACTIVE INGREDIENTS: Allantoin 0.15 g/3 1
INACTIVE INGREDIENTS: Water; Glycerin

ACTIVE INGREDIENT

Active ingredient: Allantoin 0.5%

INACTIVE INGREDIENT

Inactive ingredients:
Aqua/Water/Eau, Glycerin, Dipropylene Glycol, Butylene Glycol, Aloe Barbadensis Leaf Extract, Niacinamide, Oryza Sativa (Rice) Extract, Oryza Sativa (Rice) Bran Extract, Camellia Sinensis Leaf Extract, Ceratonia Siliqua Gum, Beta-Glucan, Chondrus Crispus (Carrageenan), Algae Extract, Cyamopsis Tetragonoloba (Guar) Gum, Potassium Chloride, Glucose, Rose Extract, Dipeptide Diaminobutyroyl Benzylamide Diacetate, Pearl Powder, Collagen, Tocopheryl Acetate, Disodium EDTA, 1,2-Hexanediol, Ubiquinone, Chamomilla Recutita (Matricaria) Extract, Diamond Powder, Fragrance/Parfum

PURPOSE

Purpose: Skin Protectant

WARNINGS

Warnings: For external use only.

KEEP OUT OF REACH OF CHILDREN

INDICATIONS & USAGE

Indications and Usage:
After cleansing, place mask on your face. Leave it on for 20-30 minutes. Gently remove the mask and lightly massage any remaining serum into your skin. Do not rinse.

DOSAGE & ADMINISTRATION

Dosage and Administration: Use at least twice a week.